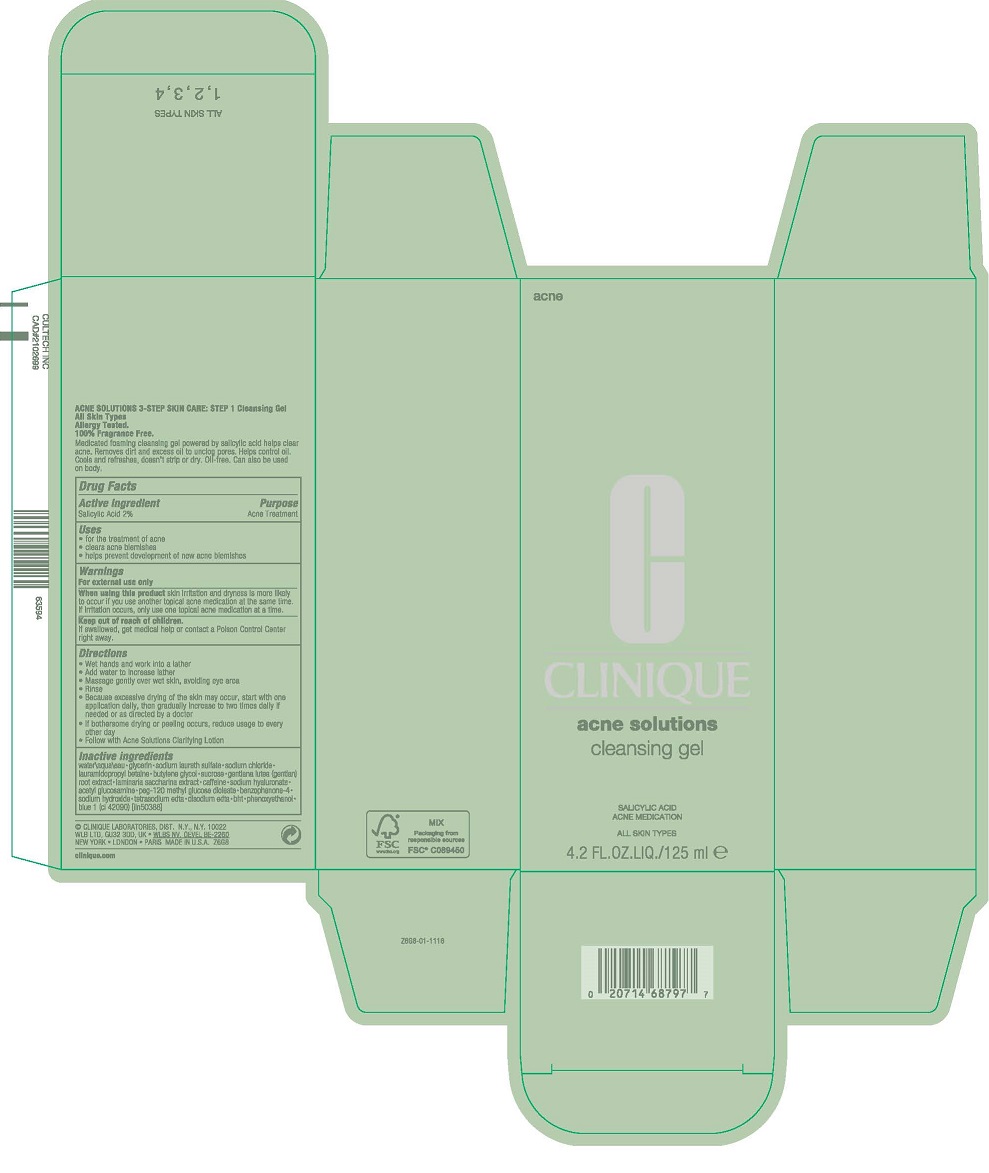 DRUG LABEL: ACNE CLEANSING
NDC: 49527-045 | Form: GEL
Manufacturer: CLINIQUE LABORATORIES LLC
Category: otc | Type: HUMAN OTC DRUG LABEL
Date: 20230830

ACTIVE INGREDIENTS: SALICYLIC ACID 20 mg/1 mL
INACTIVE INGREDIENTS: EDETATE DISODIUM ANHYDROUS; WATER; GLYCERIN; SODIUM LAURETH-3 SULFATE; SODIUM CHLORIDE; LAURAMIDOPROPYL BETAINE; BUTYLENE GLYCOL; SUCROSE; GENTIANA LUTEA ROOT; SACCHARINA LATISSIMA; CAFFEINE; HYALURONATE SODIUM; N-ACETYLGLUCOSAMINE; PEG-120 METHYL GLUCOSE DIOLEATE; SULISOBENZONE; SODIUM HYDROXIDE; EDETIC ACID; EDETATE SODIUM; BUTYLATED HYDROXYTOLUENE; PHENOXYETHANOL; FD&C BLUE NO. 1

ACNE SOLUTIONS CLEANSING GEL

Drug Facts

Active Ingredient

Salicylic Acid 2%

Purpose

Acne Treatment

Uses

- treats acne
- clears acne blemishes
- helps prevent development of new acne blemishes

Warnings

For external use only

When using this product skin irritation and dryness is more likely to occur if you use another topical acne medication at the same time. If irritation occurs, only use one topical acne medication at a time.

Keep out of reach of children.

If product is swallowed, get medical help or contact a Poison Control Center right away.

Directions

- Wet hands and work into a lather
- Add water to increase lather
- Massage gently over wet skin, avoiding eye area
- Rinse
- Use A.M. and P.M.
- If bothersome drying or peeling occurs, reduce usage to every other day
- Follow with Acne Solutions Clarifying Lotion

Inactive ingredients

water\aqua\eau [] glycerin [] sodium laureth sulfate [] sodium chloride [] lauramidopropyl betaine [] butylene glycol [] sucrose [] gentiana lutea (gentian) root extract [] laminaria saccharina extract [] caffeine [] sodium hyaluronate [] acetyl glucosamine [] peg-120 methyl glucose dioleate [] benzophenone-4 [] sodium hydroxide [] tetrasodium edta [] disodium edta [] bht [] phenoxyethanol [] blue 1 (ci 42090) <iln50388>

Other information

Protect the product in this container from excessive heat and direct sun

PRINCIPAL DISPLAY PANEL - 125 mL Tube Carton

CLINIQUE

acne solutions
cleansing gel

SALICYLIC ACID
ACNE MEDICATION

ALL SKIN TYPES

4.2 FL.OZ.LIQ./125 ml e